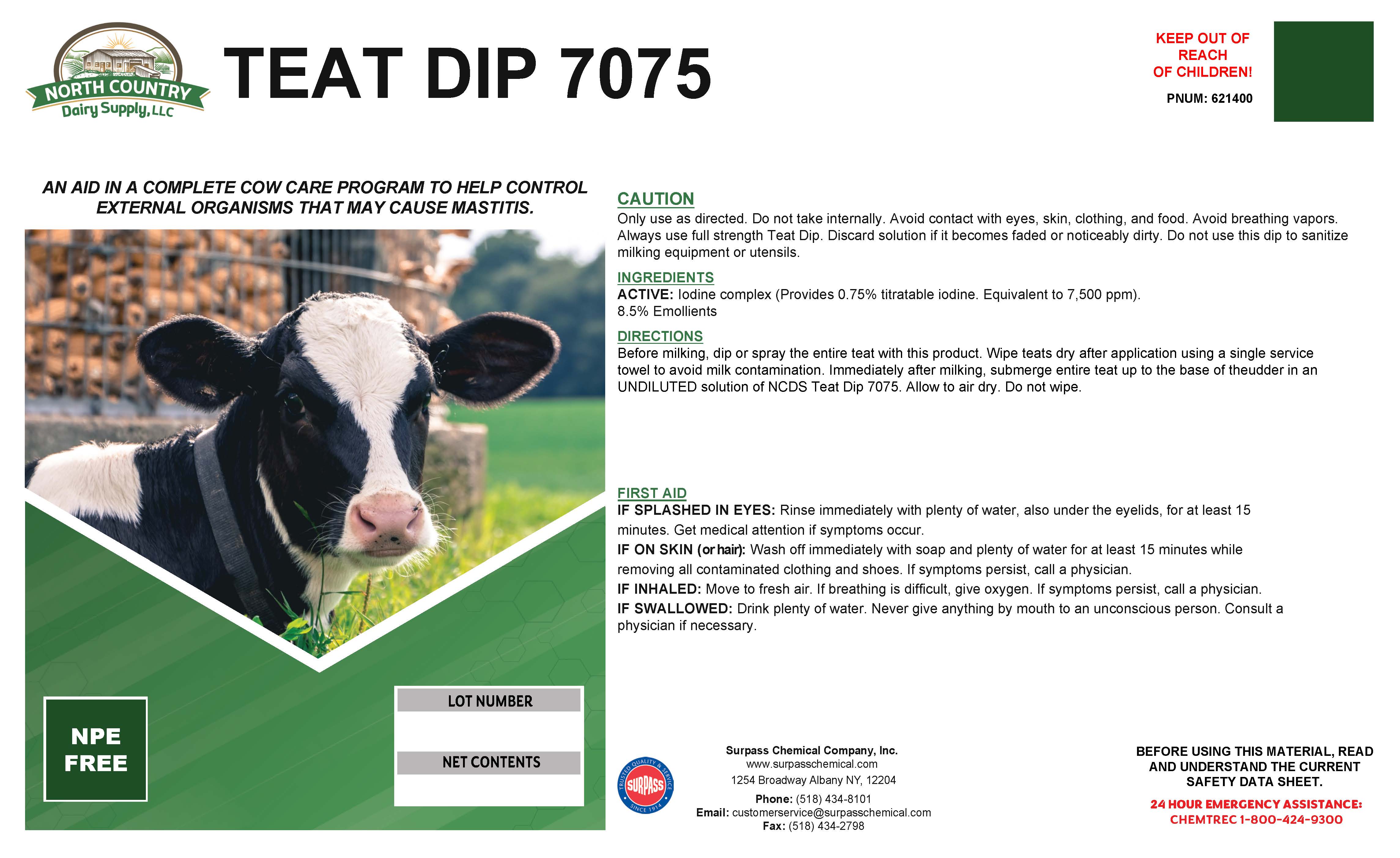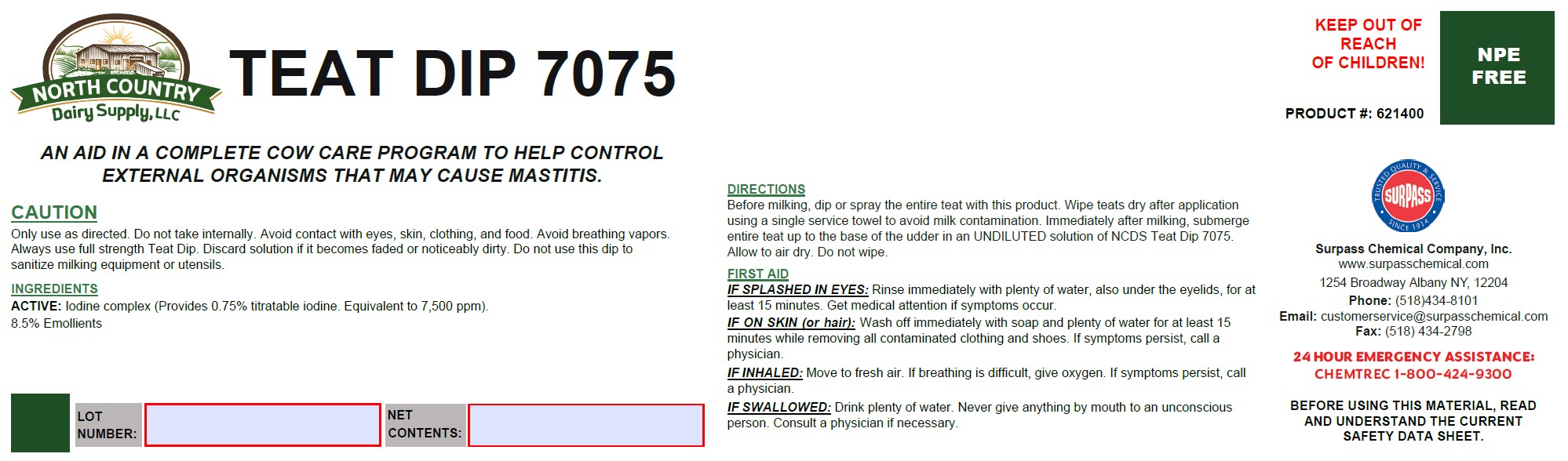 DRUG LABEL: Teat Dip 7075
NDC: 86067-0114 | Form: SOLUTION
Manufacturer: Surpass Chemical Company, Inc.
Category: animal | Type: OTC ANIMAL DRUG LABEL
Date: 20240617

ACTIVE INGREDIENTS: IODINE 0.0349 kg/1 kg
INACTIVE INGREDIENTS: WATER 0.8376 kg/1 kg; C9-11 PARETH-8 0.0375 kg/1 kg; GLYCERIN 0.085 kg/1 kg; TRISODIUM CITRATE DIHYDRATE 0.005 kg/1 kg

Teat Dip 7075

DESCRIPTION

TEAT DIP 7075

An aid in a complete cow care program to help control external organisms that may cause mastitis. PRODUCT #: 621400

DIRECTIONS:
Before milking, dip or spray the entire teat with this product. Wipe teats dry after application using a single service towel to avoid milk contamination. Immediately after milking, submerge entire teat up to the base of the udder in an UNDILUTED solution of a NCDS TD7075. Allow to air dry. Do not wipe.

GENERAL PRECAUTIONS

CAUTION:
Only use as directed. Do not take internally. Avoid contact with eyes, skin, clothing, and food. Avoid breathing vapors.
Always use full strength teat dip. Discard solution if it becomes faded or noticeably dirty. Do not use this dip to sanitize milking equipment or utensils.

ACTIVE INGREDIENT

INGREDIENTS:
ACTIVE: Iodine complex (Provides 0.75% titratable iodine. Equivalent to 7,500 ppm).

8.5% Emollients

OTHER SAFETY INFORMATION

FIRST AID:
IF SPLASHED IN EYES: Rinse immediately with plenty of water, also under the eyelids, for at least 15 minutes. Get medical attention if symptoms occur.
IF ON SKIN (or hair): Wash off immediately with soap and plenty of water for at least 15 minutes while removing all contaminated clothing and shoes. If symptoms persist, call a physician.
IF INHALED: Move to fresh air. If breathing is difficult, give oxygen. If symptoms persist, call a physician.
IF SWALLOWED: Drink plenty of water. Never give anything by mouth to an unconscious person. Consult a physician if necessary.

Surpass Chemical Company, Inc.
www.surpasschemical.com 24 HOUR EMERGENCY ASSISTANCE:
Phone: (518) 434-8101 1254 Broadway CHEMTREC 1-800-424-9300
Fax: (518) 434-2798 Albany NY, 12204
Email: customerservice@surpasschemical.com

KEEP OUT OF REACH OF CHILDREN!

SAFE HANDLING WARNING

BEFORE USING THIS MATERIAL, READ AND
UNDERSTAND THE CURRENT SAFETY DATA SHEET.